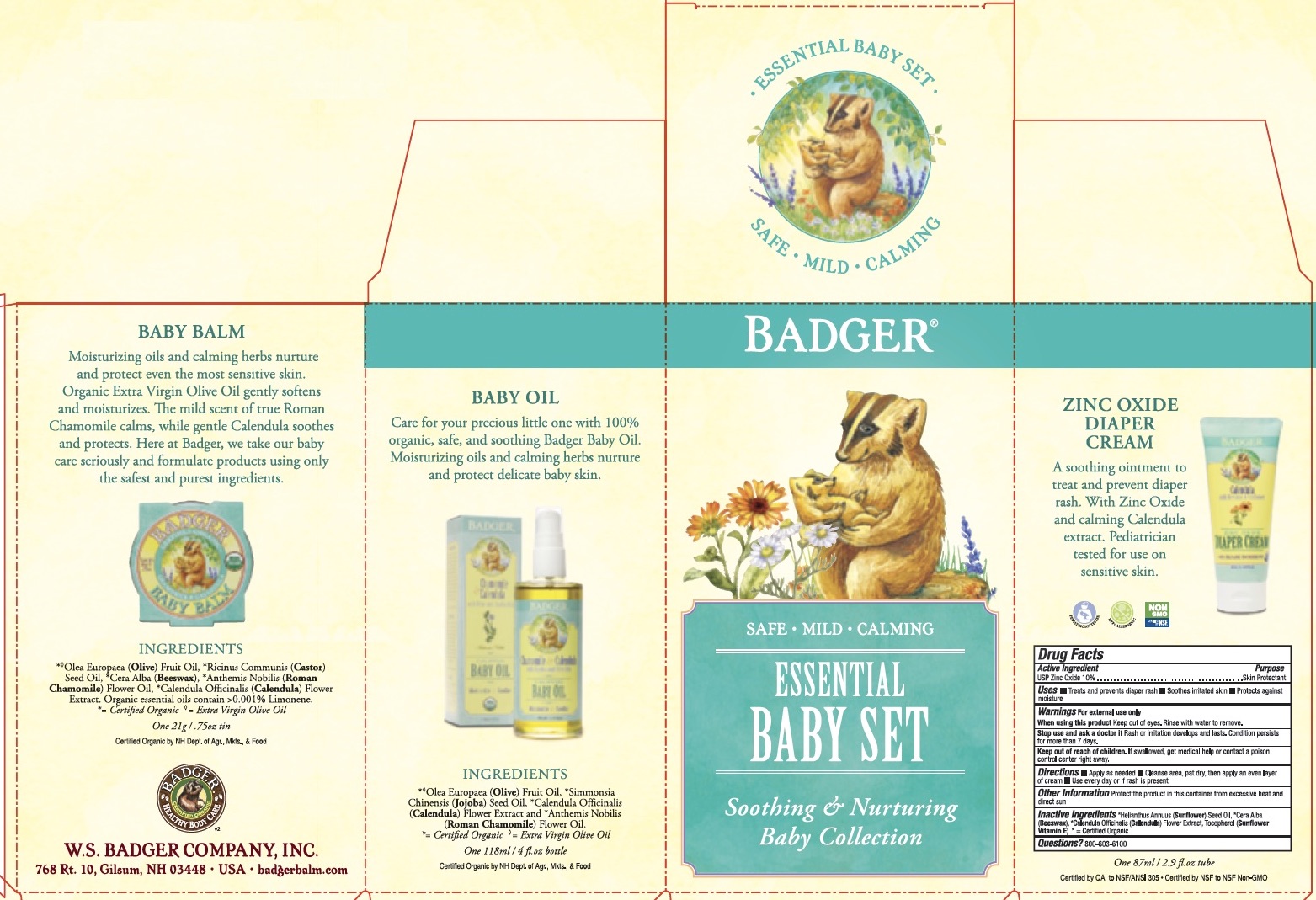 DRUG LABEL: Badger Essential Baby Set
NDC: 62206-3360 | Form: KIT | Route: TOPICAL
Manufacturer: W.S. Badger Company, Inc.
Category: otc | Type: HUMAN OTC DRUG LABEL
Date: 20221219

ACTIVE INGREDIENTS: ZINC OXIDE 10 g/100 mL
INACTIVE INGREDIENTS: SUNFLOWER OIL; TOCOPHEROL; HIPPOPHAE RHAMNOIDES FRUIT; CALENDULA OFFICINALIS FLOWER; YELLOW WAX

Set EOM's; Badger ® Essential Baby Set

Active Ingredient

Zinc oxide 10%

Purpose

Skin Protectant

Keep out of reach of children. If swallowed, get medical help or contact a poison control center right away

Uses

■ Treats and prevents diaper rash ■ Soothes irritated skin ■ Protects against moisture

Directions

■ Cleanse area, pat dry, then apply an even layer of cream ■ Use every day or if rash is present

INACTIVE INGREDIENT

*Helianthus Annuus (Sunflower) Seed Oil, *Cera Alba (Beeswax), *Calendula Officinalis (Calendula) Flower Extract, Tocopherol (Sunflower Vitamin E). * = Certified Organic

Warnings

For external use only

When using this product: Keep out of eyes. Rinse with water to remove.

Stop use and ask a doctor if: Rash or irritation develops and lasts. Condition persists for more than 7 days.

PACKAGE LABEL

Diaper Cream

Keeps skin soft and dry. Zinc Oxide treats and prevents diaper rash.